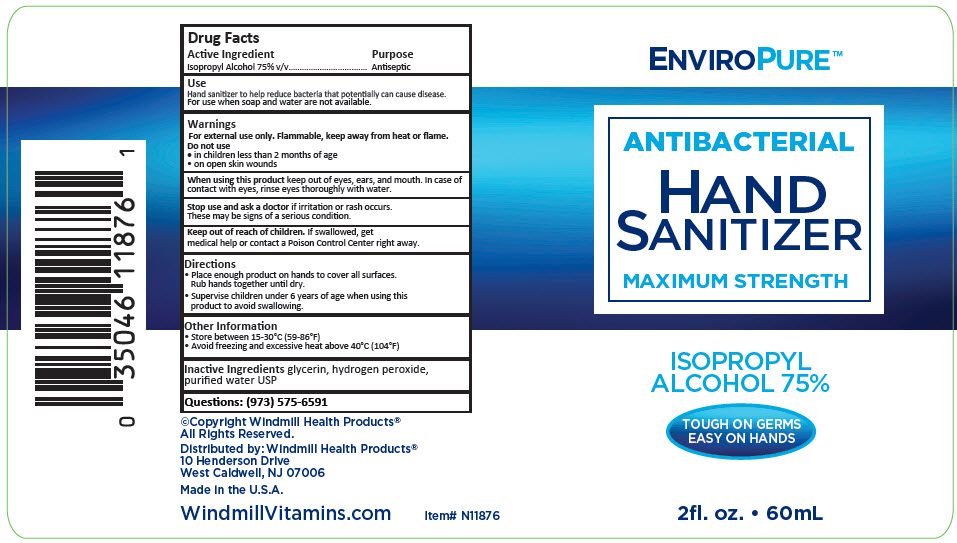 DRUG LABEL: EnviroPure Antibacterial Hand Sanitizer Maximum Strength
NDC: 74154-009 | Form: LIQUID
Manufacturer: Windmill Health Products, LLC
Category: otc | Type: HUMAN OTC DRUG LABEL
Date: 20210209

ACTIVE INGREDIENTS: ISOPROPYL ALCOHOL 75 mL/100 mL
INACTIVE INGREDIENTS: Glycerin; Hydrogen Peroxide; Water

EnviroPure™ Antibacterial Hand Sanitizer Maximum Strength

Drug Facts

Active Ingredient

Isopropyl Alcohol 75% v/v

Purpose

Antiseptic

Use

Hand sanitizer to help reduce bacteria that potentially can cause disease.

For use when soap and water are not available.

Warnings

For external use only. Flammable, keep away from heat or flame.

Do not use

- in children less than 2 months of age
- on open skin wounds

When using this product keep out of eyes, ears, and mouth. In case of contact with eyes, rinse eyes thoroughly with water.

Stop use and ask a doctor if irritation or rash occurs.

These may be signs of a serious condition.

Keep out of reach of children. If swallowed, get medical help or contact a Poison Control Center right away.

Directions

- Place enough product on hands to cover all surfaces.
  Rub hands together until dry.
- Supervise children under 6 years of age when using this product to avoid swallowing.

Other Information

- Store between 15-30°C (59-86°F)
- Avoid freezing and excessive heat above 40°C (104°F)

Inactive Ingredients

glycerin, hydrogen peroxide, purified water USP

Questions

(973) 575-6591

Distributed by: Windmill Health Products®
10 Henderson Drive
West Caldwell, NJ 07006

PRINCIPAL DISPLAY PANEL - 60 mL Bottle Label

ENVIROPURE™

ANTIBACTERIAL

HAND
SANITIZER

MAXIMUM STRENGTH

ISOPROPYL
ALCOHOL 75%

TOUGH ON GERMS
EASY ON HANDS

2fl. oz. • 60mL